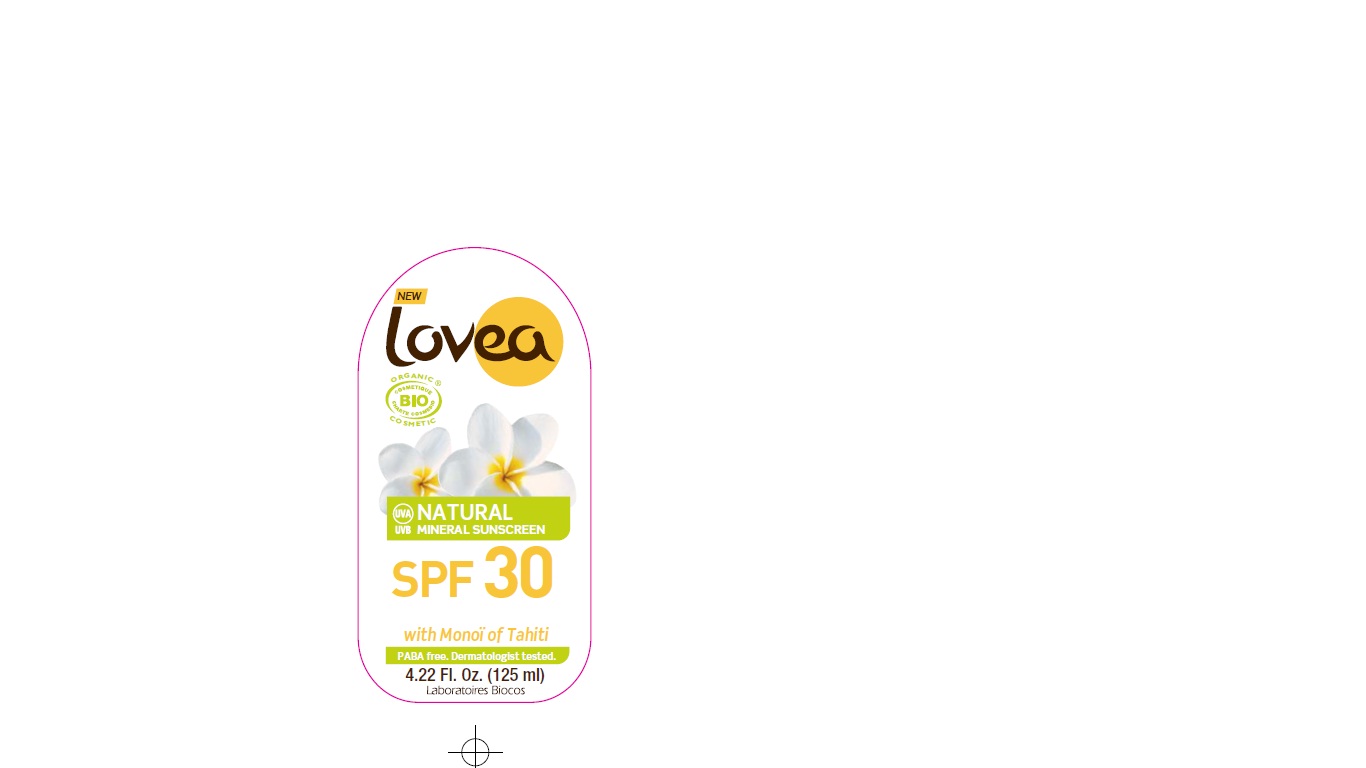 DRUG LABEL: LOVEA
NDC: 76363-029 | Form: CREAM
Manufacturer: Laboratoires Biocos
Category: otc | Type: HUMAN OTC DRUG LABEL
Date: 20120426

ACTIVE INGREDIENTS: Titanium dioxide 12.1 g/100 g
INACTIVE INGREDIENTS: Dicaprylyl carbonate; Polyglyceryl-3 Diisostearate; Stearic Acid; Aluminum hydroxide; MEDIUM-CHAIN TRIGLYCERIDES; Coco-caprylate; Coco-caprylate/caprate; Alcohol; ARGAN OIL; CAPRYLYL/CAPRYL OLIGOGLUCOSIDE; COCONUT OIL; GARDENIA TAITENSIS FLOWER; ZANTHOXYLUM ARMATUM VAR. ARMATUM FRUIT; oleyl alcohol; LINALOOL, (+/-)-; LIMONENE, (+)-; P-METHYL ANISOLE; BENZYL BENZOATE; METHYL BENZOATE; BENZYL SALICYLATE; FARNESOL

Natural mineral Sunscreen SPF 30

Drug Facts

Active ingredients Purpose
Titanium dioxide (12,1%) ........................................................................Sunscreen

Use
• Helps prevent sunburn • Higher SPF gives more sunburn protection • Provides
high protection against sunburn

Warnings
For external use only. When using this product keep out of eyes. Rinse with water
to remove. Stop use and ask a doctor if rash or irritation develops and lasts. Keep
out of the reach of children. If swallowed, get medical help or contact a Poison
Control Center right away.

Directions
• Apply generously and evenly to all areas 15 minutes before sun exposure • Spray on
hands to apply to face • Reapply at frequent intervals and after swimming, sweating
or towel drying • Ask a doctor before use on children under six months of age

Other information
Sun alert: Limiting sun exposure, wearing protective clothing, and using sunscreens
may reduce the risks of skin aging, skin cancer, and other harmful effects of the sun.

Inactive ingredients
DICAPRYLYL CARBONATE, CAPRYLIC/CAPRIC TRIGLYCERIDE, COCO-CAPRYLATE,
COCO-CAPRYLATE/CAPRATE, ALCOHOL*, ARGANIA SPINOSA KERNEL OIL*, ALUMINIUM HYDROXIDE,
STEARIC ACID, POLYGLYCERYL-3 DIISOSTEARATE, PARFUM (FRAGRANCE), COCOS NUCIFERA
(COCONUT) OIL, GARDENIA TAHITENSIS FLOWER, OLEYL ALCOHOL, ZANTHOXYLUM ALATUM FRUIT
EXTRACT. *Ingredients from organic farming